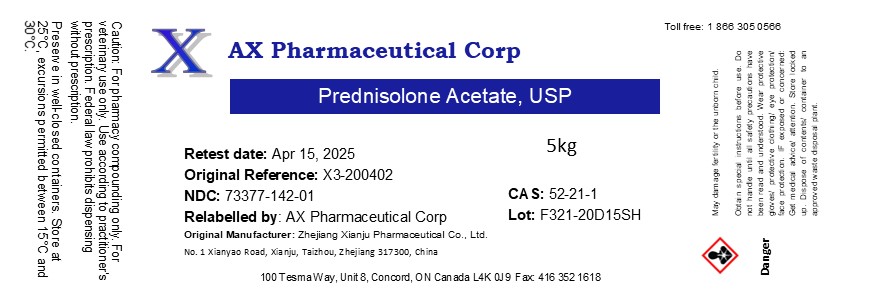 DRUG LABEL: Prednisolone Acetate
NDC: 73377-142 | Form: POWDER
Manufacturer: AX Pharmaceutical Corp
Category: other | Type: BULK INGREDIENT - ANIMAL DRUG
Date: 20231205

ACTIVE INGREDIENTS: PREDNISOLONE ACETATE 1 kg/1 kg

Prednisolone Acetate